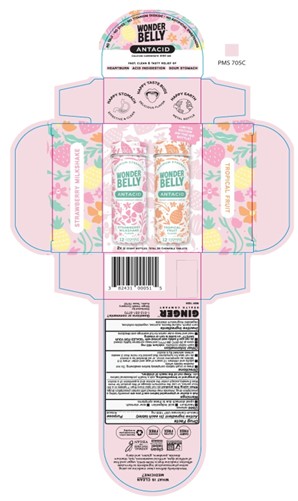 DRUG LABEL: WONDERBELLY MAXIMUM STRENGTH ANTACID
NDC: 82431-191 | Form: KIT | Route: ORAL
Manufacturer: Ginger Health Company
Category: otc | Type: HUMAN OTC DRUG LABEL
Date: 20250201

ACTIVE INGREDIENTS: CALCIUM CARBONATE 1000 mg/1 1; CALCIUM CARBONATE 1000 mg/1 1
INACTIVE INGREDIENTS: SUCROSE; MICROCRYSTALLINE CELLULOSE; MAGNESIUM STEARATE; STARCH, CORN; SUCROSE; STARCH, CORN; CELLULOSE, MICROCRYSTALLINE; MAGNESIUM STEARATE

Strawberry Milkshake + Tropical Fruit Antacids Kit- Multi-Pack

Active Ingredient (per tablet)

Calcium Carbonate 1000mg

Purpose

Antacid

Uses

relieves

- hearburn
- acid indigestion
- sour stomach
- upset stomach associated with these symptoms

Warnings

Ask a doctor or pharmacist before use if you are

presently taking a prescription drug. Antacids may interact with certain prescription drugs.

When using this product

do not take more than 7 tablets in a 24-hour period, or use the maximum dosage of this product for more than 2 weeks, except under the advice and supervision of a doctor

If pregnant or breastfeeding,

ask a health professional before use

Keep out of reach of children.

Directions

- chew or crush tablets completely before swallowing. Do not swallow tablets whole.
- adults and children 12 years of age and over: chew 2-3 tablets as symptoms occur, or as directed by a doctor
- do not take for symptoms that persist more than 2 weeks unless advised by a doctor

Other Information

- each tablet contains: calcium 400 mg
- store at 20-25°C (68-77°F) and keep container tightly closed
- do not use if safety seal on bottle printed with "SEALED FOR YOUR SAFETY" is torn or missing

Inactive Ingredients

corn starch, natural flavors, sucrose, vegetable cellulose, vegetable magnesium stearate

Questions or Comments

call 1-512-551-9770

Distributed by:

Ginger Health Company

Austin, Texas 78702

Principal Display Panel

No Talc, No Dyes, No Titanium Dioxide, No Artifical Sweeteners

WONDERBELLY

ANTACID

Calcium Carbonate 1000 MG

Fast, Clean & Tasty Relief of

Heartburm, Acid Indigestion, Sour Stomach

2x12 cout bottles, total 24 chewable tablets